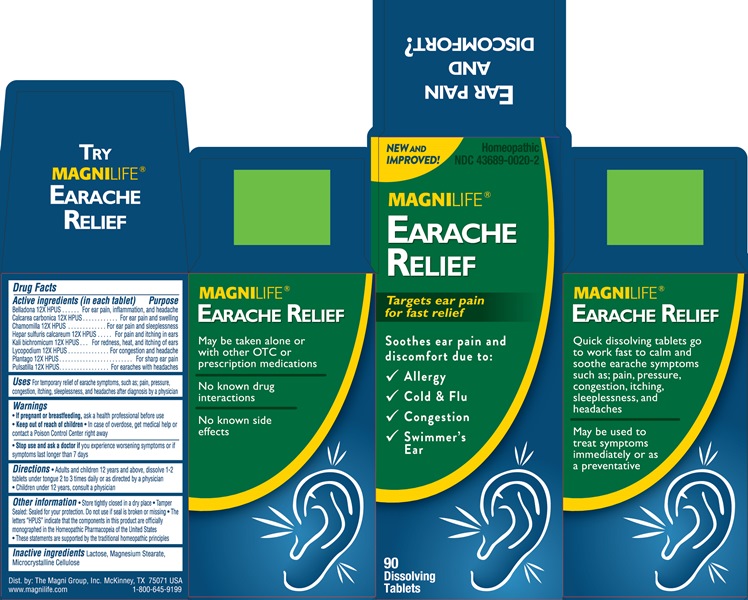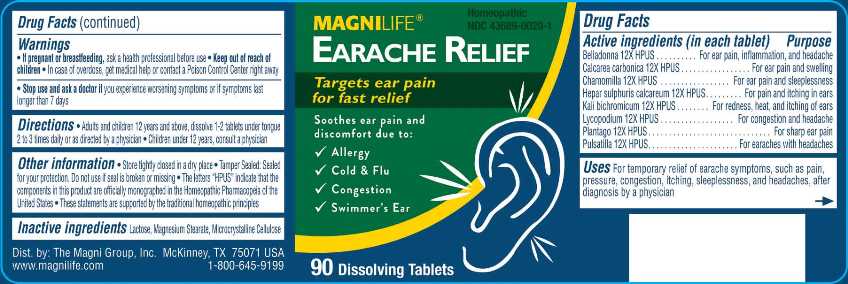 DRUG LABEL: Earache Relief
NDC: 43689-0020 | Form: TABLET
Manufacturer: The Magni Company
Category: homeopathic | Type: HUMAN OTC DRUG LABEL
Date: 20241105

ACTIVE INGREDIENTS: ATROPA BELLADONNA 12 [hp_X]/1 1; OYSTER SHELL CALCIUM CARBONATE, CRUDE 12 [hp_X]/1 1; MATRICARIA CHAMOMILLA WHOLE 12 [hp_X]/1 1; CALCIUM SULFIDE 12 [hp_X]/1 1; POTASSIUM DICHROMATE 12 [hp_X]/1 1; LYCOPODIUM CLAVATUM SPORE 12 [hp_X]/1 1; PLANTAGO MAJOR WHOLE 12 [hp_X]/1 1; PULSATILLA VULGARIS WHOLE 12 [hp_X]/1 1
INACTIVE INGREDIENTS: LACTOSE; MAGNESIUM STEARATE; CELLULOSE, MICROCRYSTALLINE

Drug Facts:

ACTIVE INGREDIENTS:

Belladonna 12X, Calcarea Carbonica 12X, Chamomilla 12X, Hepar Sulphuris Calcareum 12X, Kali Bichromicum 12X, Lycopodium Clavatum 12X, Plantago Major 12X, Pulsatilla (Vulgaris) 12X.

USES:

For temporary relief of earache symptoms, such as pain, pressure, congestion, itching, sleeplessness, and headaches, after diagnosis by a physician.

WARNINGS:

• If pregnant or breastfeeding, ask a health professional before use.

• Keep out of reach of children. In case of overdose, get medical help or contact a Poison Control Center right away.

• Stop use and ask a doctor if you experience worsening symptoms or if symptoms last longer than 7 days.

Keep out of reach of children. In case of overdose, get medical help or contact a Poison Control Center right away.

OTHER INFORMATION:

• Store tightly closed in a cool, dry place (59° - 86°F)

• Tamper sealed: Sealed for your protection. Do not use if seal is broken or missing

• The letters "HPUS" indicate that the components in this product are officially monographed in the Homeopathic Pharmacopeia of the United
States

• These statements are supported by the traditional homeopathic principles

DIRECTIONS:

Adults and children 12 years and above: dissolve 1-2 tablets under tongue, 2 to 3 times daily or as directed by a physician.

Children under 12 years, consult a physician.

INDICATIONS:

For temporary relief of earache symptoms, such as pain, pressure, congestion, itching, sleeplessness, and headaches, after diagnosis by a physician.

INACTIVE INGREDIENTS:

Lactose, Magnesium Stearate, Microcrystalline Cellulose

QUESTIONS:

Dist. by: The Magni Group, Inc. McKinney, TX 75071 USA

www.magnilife.com 1-800-645-9199

PACKAGE LABEL DISPLAY:

MAGNILIFE Homeopathic

NDC 43689-0020-1

EARACHE RELIEF

Targets ear pain
for fast relief

Soothes ear pain and
discomfort due to:
√ Allergy
√ Cold & Flu
√ Congestion
√Swimmer's Ear

90 Dissolving Tablets